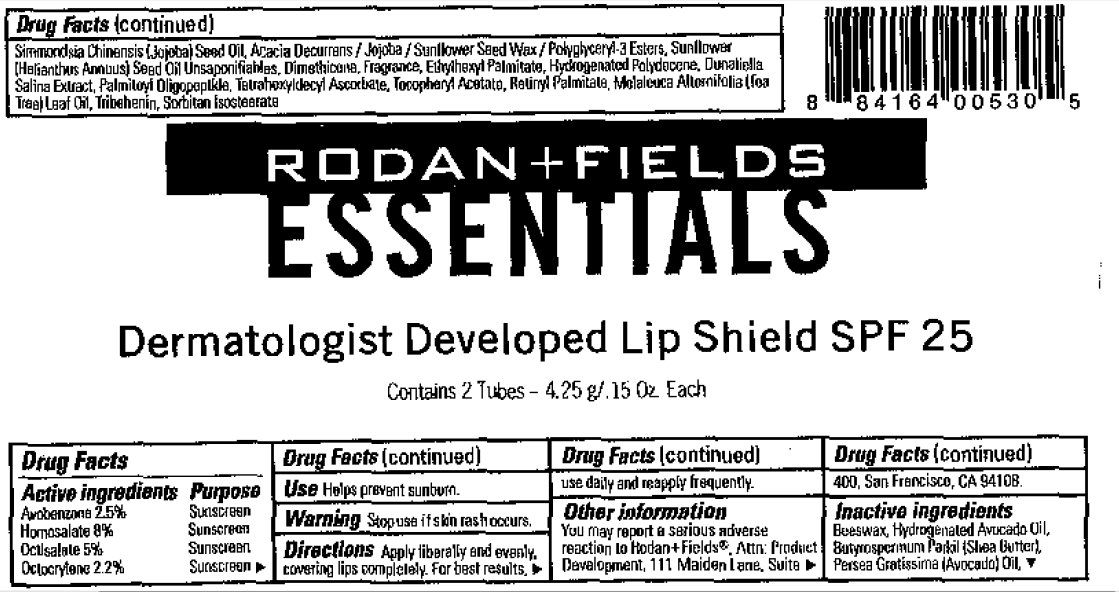 DRUG LABEL: Rodan And Fields Essentials Lip Shield SPF 25
NDC: 14222-425 | Form: LIPSTICK
Manufacturer: Rodan & Fields
Category: otc | Type: HUMAN OTC DRUG LABEL
Date: 20110622

ACTIVE INGREDIENTS: AVOBENZONE 2.5 g/100 g; HOMOSALATE 8 g/100 g; OCTISALATE 5 g/100 g; OCTOCRYLENE 2.2 g/100 g
INACTIVE INGREDIENTS: YELLOW WAX; AVOCADO OIL; SHEA BUTTER; JOJOBA OIL; HELIANTHUS ANNUUS SEED WAX; SUNFLOWER OIL; DIMETHICONE; ETHYLHEXYL PALMITATE; DUNALIELLA SALINA; TETRAHEXYLDECYL ASCORBATE; VITAMIN A PALMITATE; TRIBEHENIN

Rodan + Fields Essentials Lip Shield SPF 25

Active Ingredients Purpose
Avobenzone 2.5% Sunscreen
Homosalate 8% Sunscreen
Octisalate 5% Sunscreen
Octocrylene 2.2% Sunscreen

PURPOSE

Use Helps prevent sunburn.

Warnings Stop use if skin rash occurs.

DOSAGE AND ADMINISTRATION

Directions Apply liberally and evenly. Covering lips completely. For best result use daily and reapply frequently.

Other Information You may report a serious adverse reaction ro Hodan + Fields. Attn: Product Development, 111 Maiden Lane, Suite 400, San Francisco, CA 94108.

INACTIVE INGREDIENT

Inactive Ingredients: Beeswax, Hydrogenated Avocado Oil, Butyrospermum Parkii (Shea Butter), Persea Gratissima (Avocado) Oil, Simmondsia Chinensis (Jojoba) Seed Oil, Acacia Decurrens / Jojoba / Sunflower Seed Wax / Polyglyceryl-3 Esters, Sunflower (Helianthus Annuus) Seed Oil Unsaponifiables, Dimethicone, Fragrance, Ethylhexyl Palmitate, Hydrogenated Polydecane, Dunaliella Salina Extract, Palmiloyl Oligopeplkle, Tetrahexyldecyl Ascorbate, Tocopheryl Acetate, Retinyl Palmitate, Molaleuca Altosnilolia (Sea Tree) Leaf Oil, Tribehenin, Sorbitan Isostearate.

PACKAGE LABEL

8 84164 00530 5 RODAN+FIELDS ESSENTIALS Dermatologist Developed Lip Shield SPF 25 Contains 2 Tubes - 4.25 g/ . 15 Oz. Each